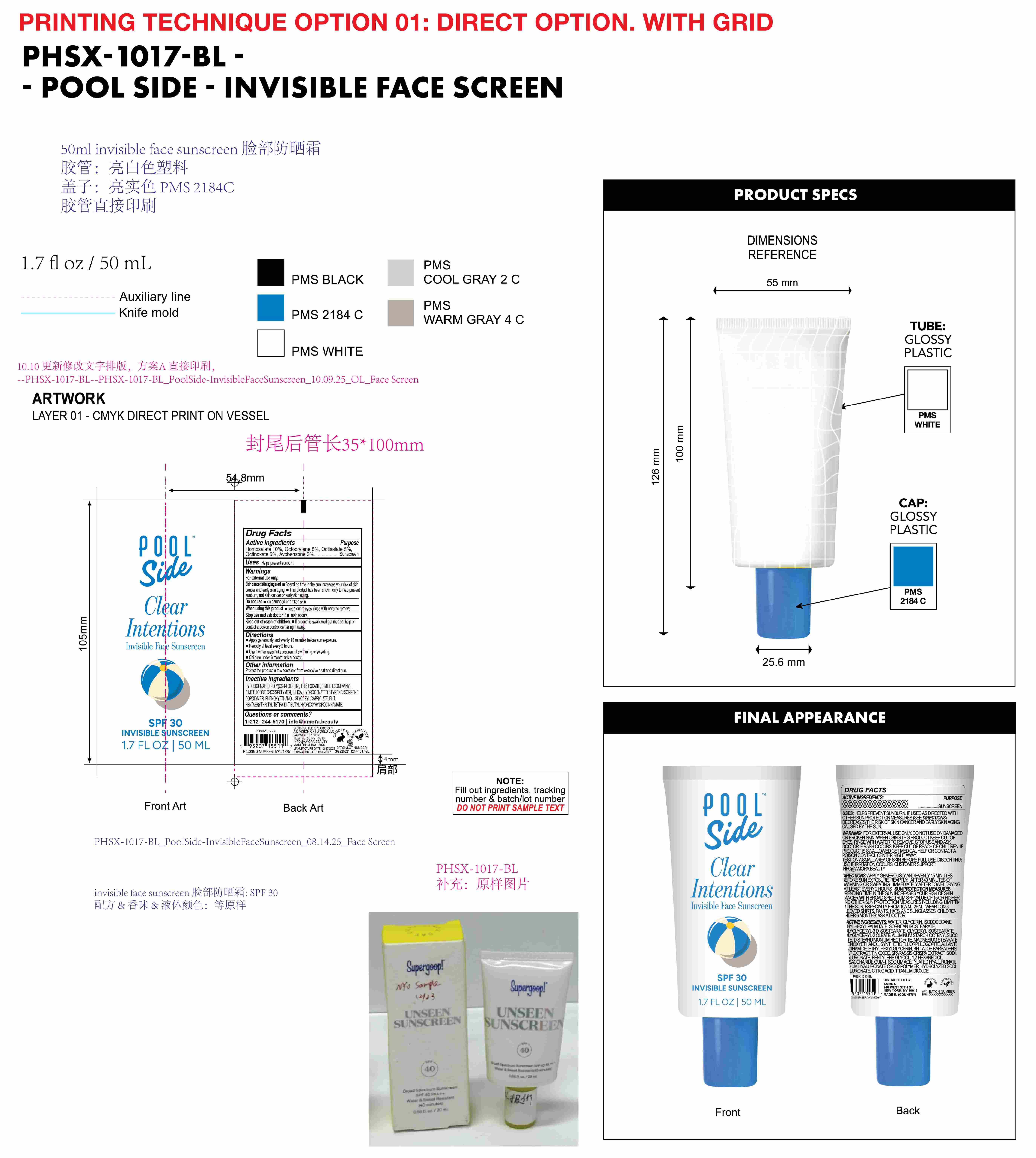 DRUG LABEL: Poolside Clear  Intentions Invisible Face Sunscreen SPF 30
NDC: 85161-150 | Form: GEL
Manufacturer: Longway Technology(Guangzhou)Co.,Ltd.
Category: otc | Type: HUMAN OTC DRUG LABEL
Date: 20251204

ACTIVE INGREDIENTS: OCTISALATE 0.05 g/1 mL; AVOBENZONE 0.03 g/1 mL; HOMOSALATE 0.1 g/1 mL; OCTOCRYLENE 0.08 g/1 mL; OCTINOXATE 0.05 g/1 mL
INACTIVE INGREDIENTS: HYDROGENATED POLY(C6-14 OLEFIN; 4 CST); PHENOXYETHANOL; DIMETHICONE/VINYL DIMETHICONE CROSSPOLYMER (SOFT PARTICLE); STYRENE/ISOPRENE COPOLYMER (28:72; 210000 MW); SILICA; GLYCERYL CAPRYLATE; BHT; PENTAERYTHRITYL TETRA-DI-T-BUTYL HYDROXYHYDROCINNAMATE; TRISILOXANE

ACTIVE INGREDIENT

Homosalate 10%, Octocrylene 8%, Octisalate 5% ,Octinoxate 5%, Avobenzone 3%

PURPOSE

Sunscreen

KEEP OUT OF REACH OF CHILDREN

lf product is swallowed get medical help or contact a poison control center right away

QUESTIONS

1-212-244-5170 info@amora.beauty

OTHER SAFETY INFORMATION

Protect the product in this container from excessive heat and direct sun.

DOSAGE AND ADMINISTRATION

Apply gererously and evenly 15 minutes before sun exposure.

Reapply at least every 2 hours.

Use a water resistant sunscreen if swimming or sweating.

Children under 6 month: ask a doctor.

WARNINGS

For external use only.

Skin cancer/skin aging alert.

Spending time in the sun increases your risk of skin cancer and early skin aging.

This product has been shown only to help prevent sunburn, not skin cancer or early skin aging.

Do not use on damaged or broken skin.

When using this product keep out of eyes. rinse with water to remove.

Stop use and ask doctor if rash occurs.

Keep out of reach of children. lf product is swallowed get medical help or contact a poison control center right away

INDICATIONS AND USAGE

Helps prevent sunburn.

INACTIVE INGREDIENT

HYDROGENATED POLY(C6-14 OLEFIN), TRISILOXANE, DIMETHICONE/VINYL DIMETHICONE CROSSPOLYMER, SILICA, HYDROGENATED STYRENE/ISOPRENE COPOLYMER, PHENOXYETHANOL, GLYCERYL CAPRYLATE, BHT, PENTAERYTHRITYL TETRA-DI-t-BUTYL HYDROXYHYDROCINNAMATE